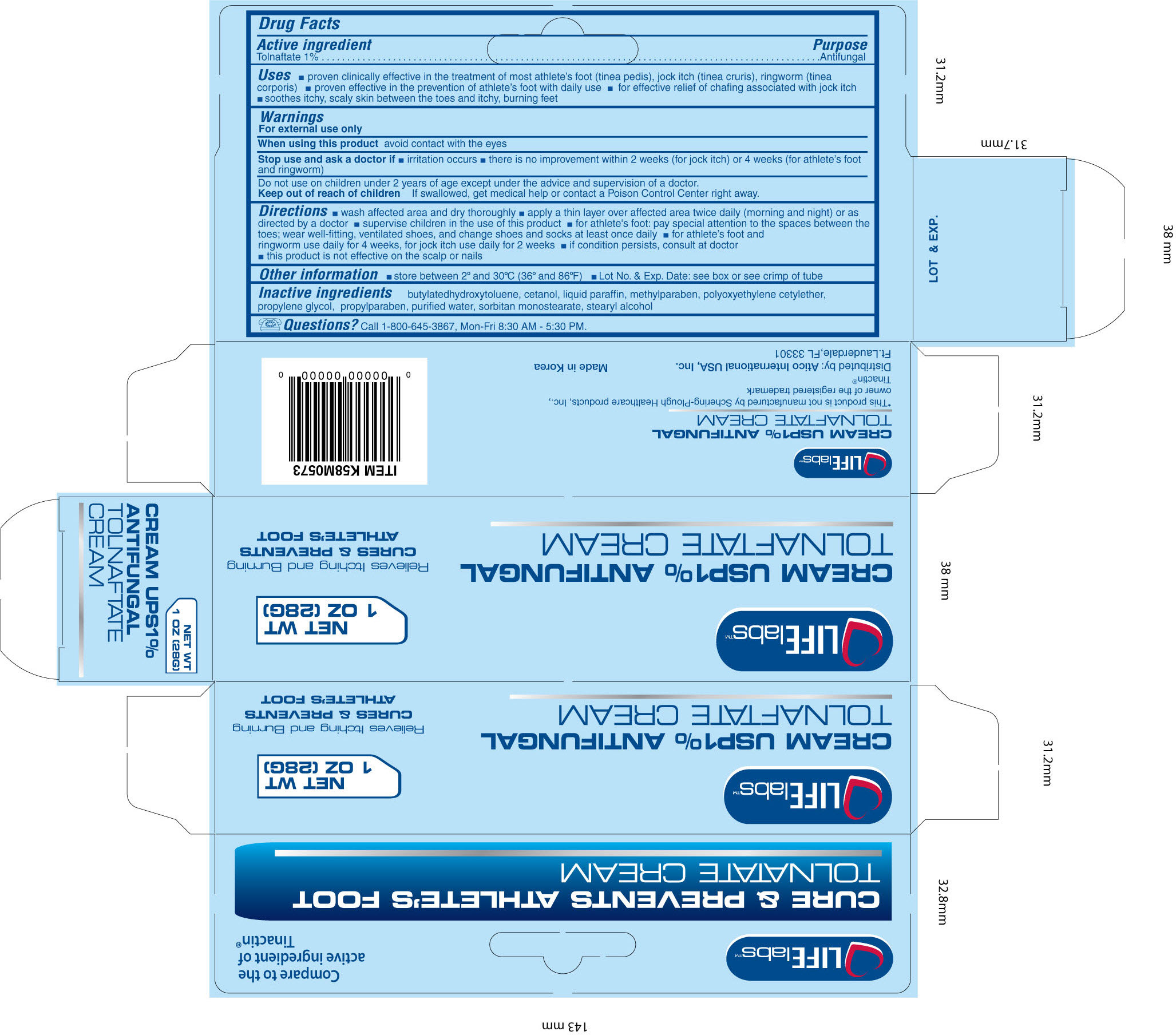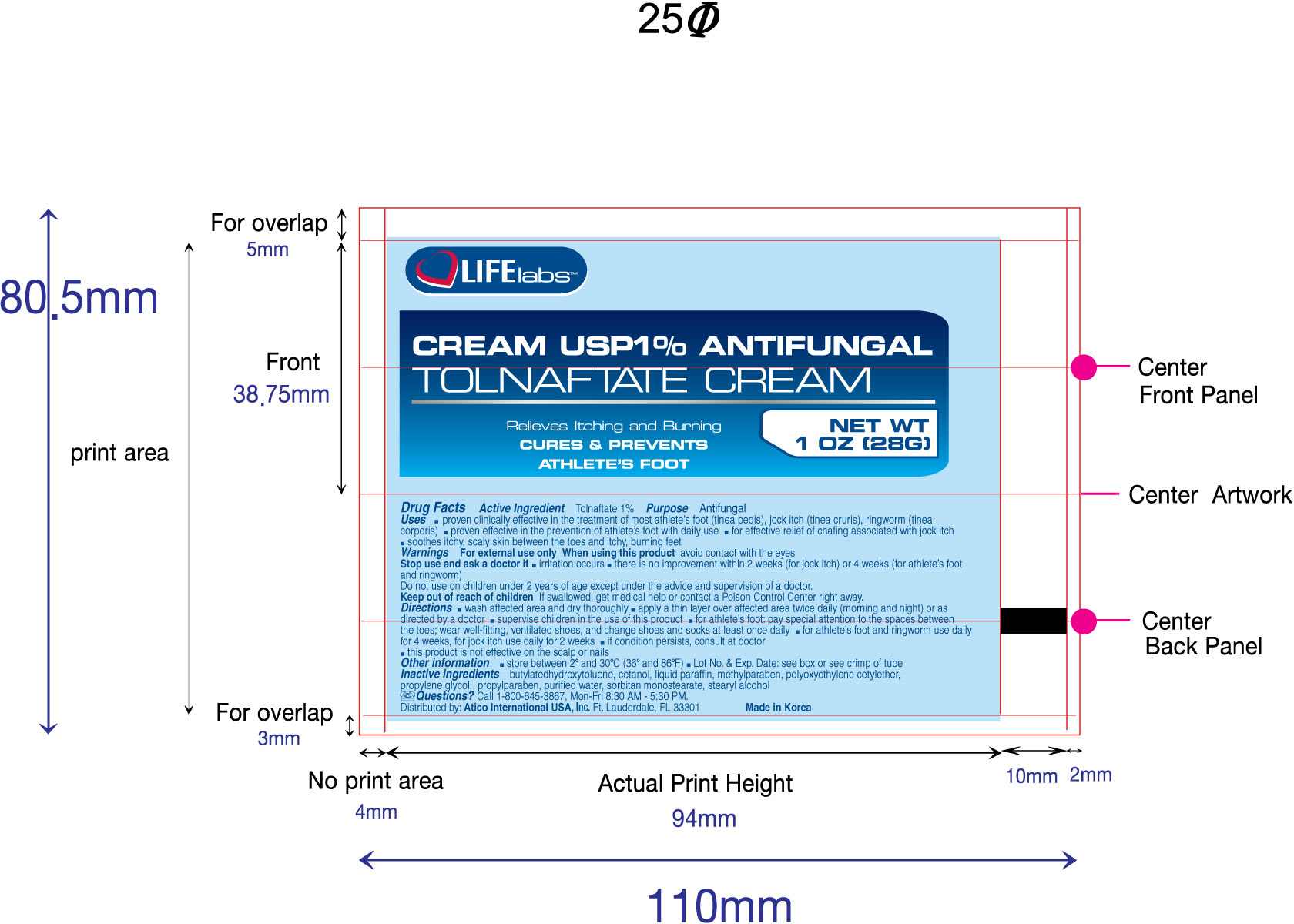 DRUG LABEL: Tolnaftate
NDC: 51852-102 | Form: CREAM
Manufacturer: LIFElabs, a Division of Atico International, USA, INC.
Category: otc | Type: HUMAN OTC DRUG LABEL
Date: 20100823

ACTIVE INGREDIENTS: Tolnaftate 10 mg/1 g
INACTIVE INGREDIENTS: Butylated Hydroxytoluene; Cetyl Alcohol; Mineral Oil; Methylparaben; Ceteth-20; Propylene Glycol; Propylparaben; Water; Sorbitan Monostearate; Stearyl Alcohol

LIFElabs, a Division of Atico International USA, INC.

Tolnaftate

Active ingredient

Tolnaftate 1%

Purpose

Antifungal

Uses

- proven clinically effective in the treatment of most athlete's foot (tinea pedis), jock itch (tinea cruris), ringworm (tinea corporis)
- proven effective in the prevention of athlete's foot with daily use
- for effective relief of chafing associated with jock itch
- soothes itchy, scaly skin between the toes and itchy, burning feet

Warnings

For external use only

When using this product avoid contact with the eyes

Stop use and ask a doctor if

- irritation occurs
- there is no improvement within 2 weeks (for jock itch) or 4 weeks (for athlete's foot and ringworm)

Do not use on children under 2 years of age except under the advice and supervision of a doctor

Keep out of reach of children

If swallowed, get medical help or contact a Poison Control Center right away

Directions

- wash affected area and dry thoroughly
- apply a thin layer over affected area twice daily (morning and night) or as directed by a doctor
- supervise children in the use of this product
- for athlete's foot: pay special attention to spaces between the toes; wear well-fitting, ventilated shoes and change shoes and socks at least once daily
- for athlete's foot and ringworm use daily for 4 weeks, for jock itch use daily for 2 weeks
- if condition persists longer consult a doctor
- this product is not effective on the scalp or nails

Other information

store between 2o and 30oC (36o and 86oF)

Lot No. and Exp. Date: see box or see crimp of tube

Inactive ingredients

butylated hydroxytoluene, cetanol, liquid paraffin, methylparaben, polyoxyethylene cetylether, propylene glycol, propylparaben, purfied water, sorbitan monostearate, stearyl alcohol

Questions?

Call 1-800-645-3867, Mon-Fri 8:30 AM - 5:30PM.